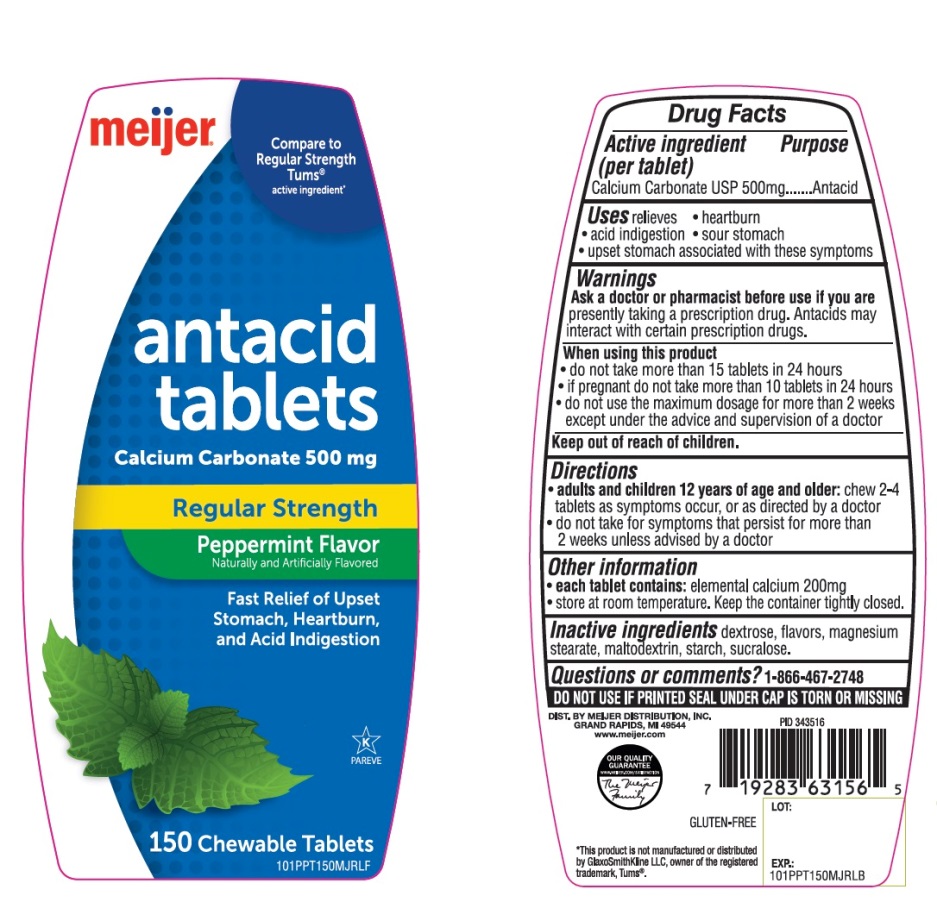 DRUG LABEL: Meijer Regular Strength

NDC: 41250-965 | Form: TABLET, CHEWABLE
Manufacturer: MEIJER DISTRIBUTION INC
Category: otc | Type: HUMAN OTC DRUG LABEL
Date: 20251024

ACTIVE INGREDIENTS: CALCIUM CARBONATE 500 mg/1 1
INACTIVE INGREDIENTS: DEXTROSE, UNSPECIFIED FORM; MAGNESIUM STEARATE; MALTODEXTRIN; STARCH, CORN; SUCRALOSE

Meijer Regular Strength Peppermint Flavor Antacid Drug Facts

Active ingredient (per tablet)

Calcium Carbonate USP 500mg

Purpose

Antacid

Uses

relieves

- heartburn
- acid indigestion
- sour stomach
- upset stomach associated with these symptoms

Warnings

Ask a doctor or pharmacist before use if you are

presently taking a prescription drug. Antacids may interact with certain prescription drugs.

When using this product

- do not take more than 15 tablets in 24 hours
- if pregnant do not take more than 10 tablets in 24 hours
- do not use the maximum dosage for more than 2 weeks except under the advice and supervision of a doctor

Directions

- adults and children 12 years of age and over:chew 2-4 tablets as symptoms occur, or as directed by a doctor. Do not swallow tablets whole.
- do not take for symptoms that persist for more than 2 weeks unless advised by a doctor

Other information

- each tablet contains: elemental calcium 200mg
- store at room temperature. Keep the container tightly closed.

Inactive ingredients

dextrose, flavor, magnesium stearate, maltodextrin, starch, sucralose.

Questions or comments?

1-866-467-2748

SAFETY SEALED:DO NOT USE IF PRINTED SEAL UNDER CAP IS TORN OR MISSING.

Principal Display Panel

meijer®

NDC#41250-965-15

Compare to Regular Strength Tums®Active Ingredient*

antacid tablets

REGULAR STRENGTH

CALCIUM CARBONATE 500mg

Peppermint

Naturally and Artificially Flavored

Fast Relief of Upset Stomach, Heartburn and Acid Indigestion

OUR QUALITY GUARANTEED

GLUTEN FREE

150 CHEWABLE TABLETS

K PAREVE

DIST BY MEIJER DISTRIBUTION, INC.

GRAND RAPIDS, MI 49544

www.meijer.com

*This product is not manufactured or distributed by GlaxoSmithKline LLC, owner of the registered trademark, Tums®.